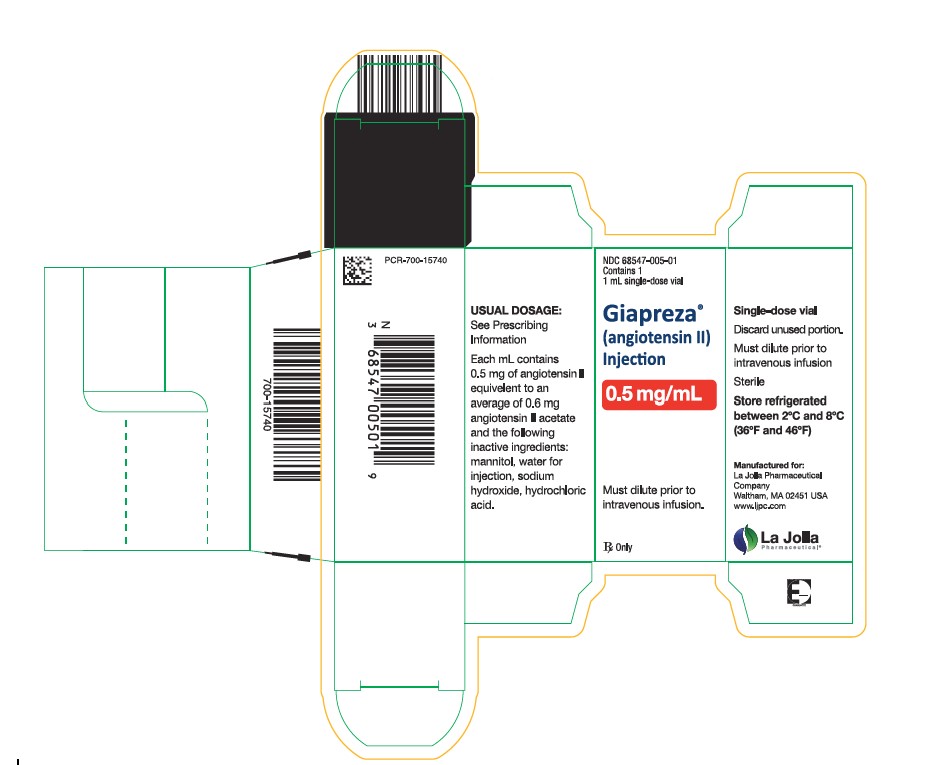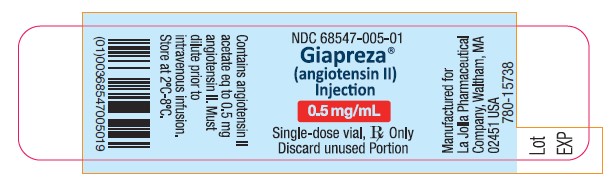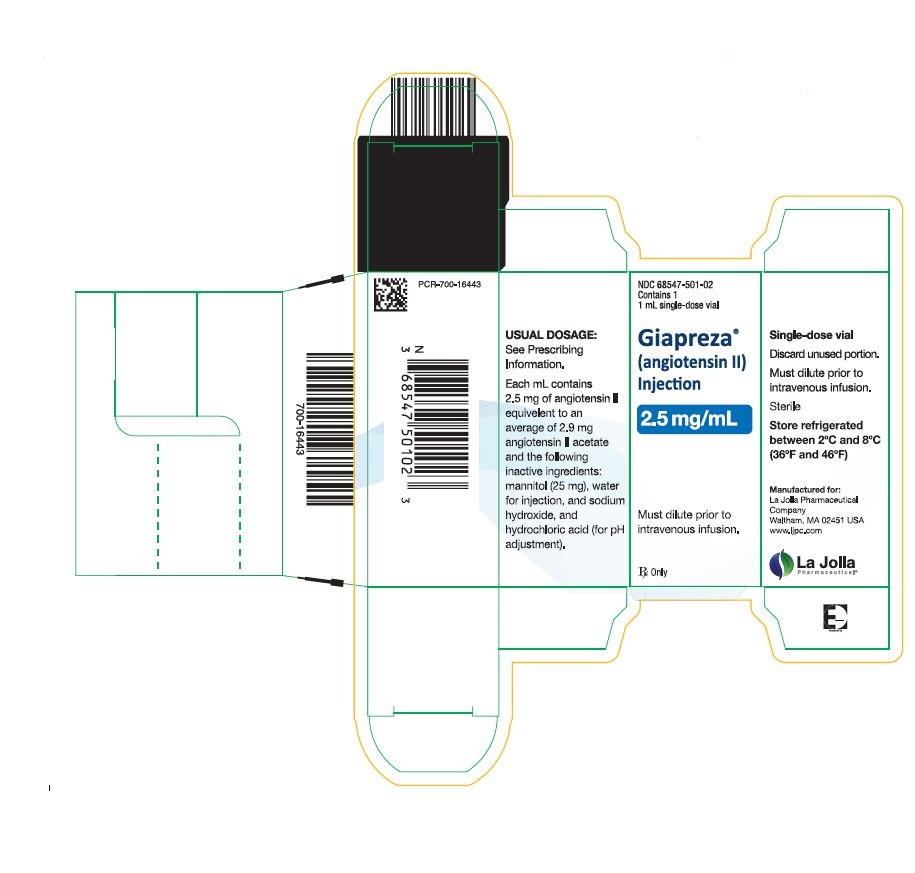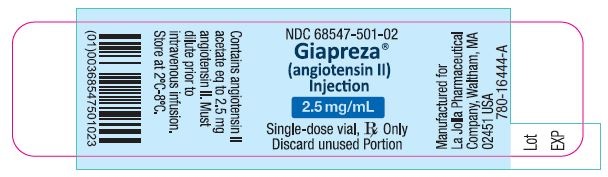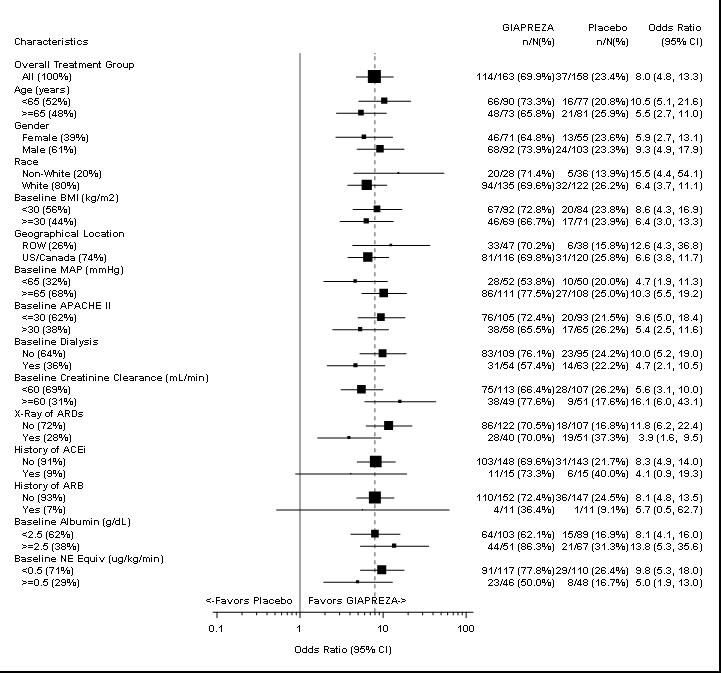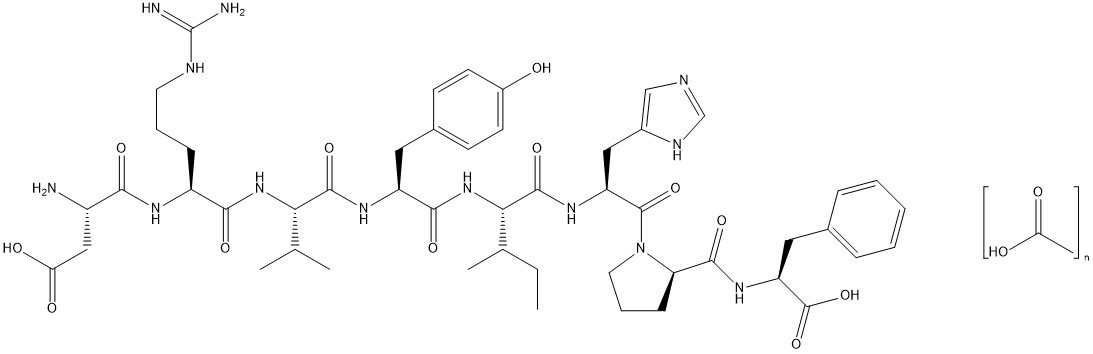 DRUG LABEL: Giapreza
NDC: 68547-501 | Form: INJECTION
Manufacturer: La Jolla Pharmaceutical Company
Category: prescription | Type: HUMAN PRESCRIPTION DRUG LABEL
Date: 20241126

ACTIVE INGREDIENTS: ANGIOTENSIN II 2.5 mg/1 mL
INACTIVE INGREDIENTS: MANNITOL 25 mg/1 mL; WATER; SODIUM HYDROXIDE; HYDROCHLORIC ACID

HIGHLIGHTS OF PRESCRIBING INFORMATION

These highlights do not include all the information needed to use GIAPREZA safely and effectively. See full prescribing information for GIAPREZA.
GIAPREZA® (angiotensin II) Injection for Intravenous Infusion
Initial U.S. Approval: 2017

RECENT MAJOR CHANGES

Dosage and Administration, Preparation (2.1) | 12/2021

1. INDICATIONS AND USAGE

GIAPREZA is a vasoconstrictor to increase blood pressure in adults with septic or other distributive shock. (1)

2. DOSAGE AND ADMINISTRATION

Dilute GIAPREZA in 0.9% sodium chloride prior to use. See Full Prescribing Information for instructions on preparation and administration of injection. Diluted solution may be stored at room temperature or under refrigeration and should be discarded after 24 hours. GIAPREZA must be administered as an intravenous infusion. (2.1)

- Start GIAPREZA intravenously at 20 nanograms (ng)/kg/min. Titrate as frequently as every 5 minutes by increments of up to 15 ng/kg/min as needed. During the first 3 hours, the maximum dose should not exceed 80 ng/kg/min. Maintenance dose should not exceed 40 ng/kg/min. Doses as low as 1.25 ng/kg/min may be used.(2.2)

3. DOSAGE FORMS AND STRENGTHS

Injection: 0.5 mg/mL and 2.5 mg/mL in a vial.

4. CONTRAINDICATIONS

None (4.1)

5. WARNINGS AND PRECAUTIONS

- There is a potential for venous and arterial thrombotic and thromboembolic events in patients who receive GIAPREZA. Use concurrent venous thromboembolism (VTE) prophylaxis. (5.1, 6.1)

6. ADVERSE REACTIONS

The most common adverse reactions reported in greater than 10% of GIAPREZA treated patients were thromboembolic events. (6.1)

To report SUSPECTED ADVERSE REACTIONS, contact La Jolla Pharmaceutical Company at 1-800-651-3861 or FDA at 1-800-FDA-1088 or www.fda.gov/medwatch.

7. DRUG INTERACTIONS

- Angiotensin converting enzyme (ACE) inhibitors
  ACE inhibitors may increase response to GIAPREZA. (7.1)
- Angiotensin II Receptor Blockers (ARB)
  ARBs may reduce response to GIAPREZA. (7.2)

FULL PRESCRIBING INFORMATION

1. INDICATIONS AND USAGE

GIAPREZA increases blood pressure in adults with septic or other distributive shock [see Clinical Studies (14)].

2. DOSAGE AND ADMINISTRATION

2.1. Preparation

Parenteral drug products should be inspected visually for particulate matter and discoloration prior to administration, whenever solution and container permit.

GIAPREZA must be administered as an intravenous infusion. GIAPREZA must be diluted in 0.9% sodium chloride prior to use. Dilute the appropriate amount of GIAPREZA in a normal saline (0.9% sodium chloride) infusion bag to achieve the desired final concentration of 5,000 ng/mL or 10,000 ng/mL.

Discard vial and any unused portion of the drug product after use.

Diluted solution may be stored at room temperature (20°C to 25°C [68°F to 77°F]) or under refrigeration (2°C to 8°C [36°F to 46°F]). Discard prepared solution after 24 hours at room temperature or under refrigeration.

2.2. Administration

The recommended starting dosage of GIAPREZA is 20 nanograms (ng)/kg/min via continuous intravenous infusion. Administration through a central venous line is recommended.

Monitor blood pressure response and titrate GIAPREZA as frequently as every 5 minutes by increments of up to 15 ng/kg/min as needed to achieve or maintain target blood pressure. Do not exceed 80 ng/kg/min during the first 3 hours of treatment. Maintenance dose should not exceed 40 ng/kg/min. Doses as low as 1.25 ng/kg/min may be used.

Once the underlying shock has sufficiently improved, down-titrate every 5 to 15 minutes by increments of up to 15 ng/kg/min based on blood pressure.

3. DOSAGE FORMS AND STRENGTHS

Injection: 0.5 mg/mL angiotensin II and 2.5 mg/mL angiotensin II in a vial.

GIAPREZA is a clear, aqueous solution.

4. CONTRAINDICATIONS

None.

5. WARNINGS AND PRECAUTIONS

5.1 Risk for Thrombosis

The safety of GIAPREZA was evaluated in 321 adults with septic or other distributive shock in a randomized, double-blind, placebo-controlled study, ATHOS-3. There was a higher incidence of arterial and venous thrombotic and thromboembolic events in patients who received GIAPREZA compared to placebo-treated patients in the ATHOS-3 study (13% vs. 5%). The major imbalance was in deep venous thromboses. Use concurrent venous thromboembolism (VTE) prophylaxis.

6. ADVERSE REACTIONS

6.1. Clinical Trials Experience

Because clinical trials are conducted under widely varying conditions, adverse reaction rates observed in the clinical trials of a drug cannot be directly compared to rates in the clinical trials of another drug and may not reflect the rates observed in practice.

ATHOS-3

The safety of GIAPREZA was evaluated in ATHOS-3 [see Warnings and Precautions(5.1)] . Patients in ATHOS-3 were receiving other vasopressors in addition to GIAPREZA or placebo, which were titrated to effect on mean arterial pressure (MAP).

Table 1 summarizes adverse reactions with an incidence of at least 4% among patients treated with GIAPREZA and with a rate of at least 1.5% higher with GIAPREZA than with placebo.

Table 1: Adverse Reactions Occurring in ≥ 4% of Patients Treated with GIAPREZA and ≥ 1.5% More Often than in Placebo-treated Patients in ATHOS-3
Adverse Event | GIAPREZA N=163 | Placebo N=158
Thromboembolic events [Including arterial and venous thrombotic events] | 21 (12.9%) | 8 (5.1%)
Deep vein thrombosis | 7 (4.3%) | 0 (0.0%)
Thrombocytopenia | 16 (9.8%) | 11 (7.0%)
Tachycardia | 14 (8.6%) | 9 (5.7%)
Fungal infection | 10 (6.1%) | 2 (1.3%)
Delirium | 9 (5.5%) | 1 (0.6%)
Acidosis | 9 (5.5%) | 1 (0.6%)
Hyperglycemia | 7 (4.3%) | 4 (2.5%)
Peripheral ischemia | 7 (4.3%) | 4 (2.5%)

7. DRUG INTERACTIONS

7.1. Angiotensin Converting Enzyme (ACE) Inhibitors

Concomitant use of angiotensin converting enzyme (ACE) inhibitors may increase the response to GIAPREZA.

7.2. Angiotensin II Receptor Blockers (ARB)

Concomitant use of angiotensin II receptor blockers (ARBs) may decrease the response to GIAPREZA.

8. USE IN SPECIFIC POPULATIONS

8.1. Pregnancy

Risk Summary

The published data on angiotensin II use in pregnant women are not sufficient to determine a drug-associated risk of adverse developmental outcomes. Animal reproduction studies have not been conducted with GIAPREZA.

All pregnancies have a background risk of birth defects, loss, or other adverse outcomes. The estimated background risk of major birth defects and miscarriage for the indicated population is unknown. In the U.S. general population, the estimated background risk of major birth defects and miscarriage in clinically recognized pregnancies is 2 to 4% and 15 to 20%, respectively.

Clinical Considerations

Disease-associated maternal and/or embryo/fetal risk

Septic or other distributive shock is a medical emergency that can be fatal if left untreated. Delaying treatment in pregnant women with hypotension associated with septic or other distributive shock is likely to increase the risk of maternal and fetal morbidity and mortality.

8.2. Lactation

Risk Summary

It is not known whether GIAPREZA is present in human milk. No data are available on the effects of angiotensin II on the breastfed child or the effects on milk production.

8.4. Pediatric Use

The safety and efficacy of GIAPREZA in pediatric patients have not been established.

8.5. Geriatric Use

In ATHOS-3, 48% of the total patient population was aged 65 years and older. There was no significant difference in safety or efficacy between patients less than 65 and those 65 years or older when treated with GIAPREZA.

10. OVERDOSAGE

Overdose of GIAPREZA would be expected to result in hypertension, necessitating close monitoring and supportive care. Effects are expected to be brief because the half-life of angiotensin II is less than one minute.

11. DESCRIPTION

Angiotensin II is a naturally occurring peptide hormone of the renin-angiotensin-aldosterone system (RAAS) that causes vasoconstriction and an increase in blood pressure. GIAPREZA is a sterile, aqueous solution of synthetic human angiotensin II for intravenous administration by infusion. Each 2.5 mg/mL vial of GIAPREZA contains 2.5 mg angiotensin II equivalent to an average of 2.9 mg angiotensin II acetate, 25 mg mannitol, and Water for Injection adjusted with sodium hydroxide and/or hydrochloric acid to pH of 5.5. Each 0.5 mg/mL vial of GIAPREZA contains 0.5 mg angiotensin II equivalent to an average of 0.6 mg angiotensin II acetate, 25 mg mannitol, and Water for Injection adjusted with sodium hydroxide and/or hydrochloric acid to pH of 5.5.

The chemical name of the synthetic angiotensin II acetate is L-Aspartyl-L-arginyl-L-valyl-Ltyrosyl-L-isoleucyl-L-histidyl-L-prolyl-L-phenylalanine, acetate salt. The counter ion acetate is present in a non-stoichiometric ratio. It is a white to off-white powder, soluble in water.

The structure of angiotensin II acetate is shown below.

Molecular formula: C 50H 71N 13O 12 ∙ (C 2H 4O 2) n; (n= number of acetate molecules; theoretical n = 3)

Average molecular weight: 1046.2 (as free base).

12. CLINICAL PHARMACOLOGY

12.1. Mechanism of Action

Angiotensin II raises blood pressure by vasoconstriction and increased aldosterone release. Direct action of angiotensin II on the vessel wall is mediated by binding to the G-protein-coupled angiotensin II receptor type 1 on vascular smooth muscle cells, which stimulates Ca^2+/calmodulin-dependent phosphorylation of myosin and causes smooth muscle contraction.

12.2. Pharmacodynamics

For the 114 (70%) patients in the GIAPREZA arm who reached the target MAP at Hour 3, the median time to reach the target MAP endpoint was approximately 5 minutes. GIAPREZA is titrated to effect for each individual patient.

12.3. Pharmacokinetics

Following intravenous infusion of angiotensin II in adults with septic or other distributive shock, serum levels of angiotensin II are similar at Baseline and Hour 3 after intravenous infusion. After 3 hours of treatment, however, the serum level of angiotensin I (the angiotensin II precursor peptide) is reduced by approximately 40%.

Distribution:

No specific studies were conducted that examined the distribution of GIAPREZA.

Metabolism and Excretion:

No specific studies were conducted that examined the metabolism and excretion of GIAPREZA.

The plasma half-life of IV administered angiotensin II is less than one minute. It is metabolized by aminopeptidase A and angiotensin converting enzyme 2 to angiotensin-(2-8) [angiotensin III] and angiotensin-(1-7), respectively in plasma, erythrocytes and many of the major organs (i.e., intestine, kidney, liver and lung). Angiotensin II type 1 receptor (AT1) mediated activity of angiotensin III is approximately 40% of angiotensin II; however, aldosterone synthesis activity is similar to angiotensin II. Angiotensin-(1-7) exerts the opposite effects of angiotensin II on AT1 receptors and causes vasodilation.

Specific Populations

No formal pharmacokinetic studies were conducted with GIAPREZA in the following specific populations.

Renal Impairment

The clearance of angiotensin II is not dependent on renal function. Therefore, the pharmacokinetics of GIAPREZA are not expected to be influenced by renal impairment.

Hepatic Impairment

The clearance of angiotensin II is not dependent on hepatic function. Therefore, the pharmacokinetics of GIAPREZA are not expected to be influenced by hepatic impairment.

Age

The effect of age was analyzed in the 163 patients receiving GIAPREZA in ATHOS-3. There were no significant differences in pharmacokinetics between age groups (< 65 years / ≥ 65 years).

Male and Female Patients

The effect of sex was analyzed in the 163 patients receiving GIAPREZA in ATHOS-3. There were no significant differences in pharmacokinetics between male and female patients.

13. NONCLINICAL TOXICOLOGY

13.1. Carcinogenesis, Mutagenesis, Impairment of Fertility

No genetic toxicity studies have been conducted with GIAPREZA. No carcinogenicity or fertility studies with GIAPREZA have been conducted in animals.

13.2. Animal Toxicology and/or Pharmacology

No animal toxicology studies were conducted with GIAPREZA.

13.3. Safety Pharmacology

In a cardiovascular safety pharmacology study in normotensive dogs, GIAPREZA doses of 150, 450, and 1,800 ng/kg (5, 15, and 60 ng/kg/min) were infused intravenously for 30 minutes each. At ≥ 450 ng/kg, GIAPREZA caused significantly elevated MAP and systemic vascular resistance, as expected. The 1,800 ng/kg dose also caused increased heart rate, increased systemic vascular resistance, increased left ventricular systolic and end-diastolic pressures, and PR interval prolongation. GIAPREZA did not significantly alter respiratory rate or cause electrocardiographic changes in QRS duration or QTc.

14. CLINICAL STUDIES

14.1. ATHOS-3

The Angiotensin II for the Treatment of High-Output Shock (ATHOS-3) trial was a double-blind study in which 321 adults with septic or other distributive shock who remained hypotensive despite fluid and vasopressor therapy were randomized 1:1 and treated with either GIAPREZA or placebo, both in addition to background vasopressor therapy. Doses of GIAPREZA or placebo were titrated to a target MAP of ≥ 75 mmHg during the first 3 hours of treatment while doses of other vasopressors were maintained. From Hour 3 to Hour 48, GIAPREZA or placebo were titrated to maintain MAP between 65 and 70 mmHg while reducing doses of other vasopressors. The primary endpoint was the percentage of subjects who achieved either a MAP ≥ 75 mmHg or a ≥ 10 mmHg increase in MAP without an increase in baseline vasopressor therapy at 3 hours.

91% of subjects had septic shock; the remaining subjects had other forms of distributive shock such as neurogenic shock. At the time of study drug administration, 97% of subjects were receiving norepinephrine, 67% vasopressin, 15% phenylephrine, 13% epinephrine, and 2% dopamine. 83% of subjects had received two or more vasopressors and 47% three or more vasopressors prior to study drug administration. 61% of subjects were male, 80% were White, 10% were Black, and 10% were other races. The median age of subjects was 64 years (range: 22-89 years). Patients requiring high doses of steroids, patients with a history of asthma or bronchospasm, and patients with Raynaud's syndrome were not included.

The primary endpoint was achieved by 70% of patients randomized to GIAPREZA compared to 23% of placebo patients; p < 0.0001 (a treatment effect of 47%). Figure 1 shows the results in all patients and in selected subgroups.

Figure 1: ATHOS-3: Primary Endpoint – Overall Result and Results in Selected Subgroups

NE Equiv = norepinephrine equivalent dose: the sum of all vasopressor doses with each vasopressor dose converted to the clinically equivalent norepinephrine dose.

Note: The figure above presents effects in various subgroups, all of which are baseline characteristics. The 95% confidence limits that are shown do not take into account the number of comparisons made and may not reflect the effect of a particular factor after adjustment for all other factors. Apparent homogeneity or heterogeneity among groups should not be over-interpreted.

In the GIAPREZA-treated group, the median time to reach the target MAP endpoint was 5 minutes. The effect on MAP was sustained for at least the first three hours of treatment. The median dose of GIAPREZA was 10 ng/kg/min at 30 minutes. Of the 114 responders at Hour 3, only 2 (1.8%) received more than 80 ng/kg/min.

Patients were not necessarily on maximum doses of other vasopressors at the time of randomization. The effect of GIAPREZA when added to maximum doses of other vasopressors is unknown.

Mortality through Day 28 was 46% on GIAPREZA and 54% on placebo (hazard ratio 0.78; 95% confidence interval 0.57 – 1.07).

16. HOW SUPPLIED/STORAGE AND HANDLING

16.1. How Supplied

GIAPREZA (angiotensin II) Injection is a clear, aqueous solution for administration by intravenous infusion supplied as a single-dose vial:

- 2.5 mg/mL vial: NDC 68547-501-02: A carton of one 1 mL single-dose vial containing 2.5 mg angiotensin II (as a sterile liquid).
- 0.5 mg/mL vial: NDC 68547-005-05: A carton of five 1 mL single-dose vials (NDC 68547-005-01) containing 0.5 mg angiotensin II (as a sterile liquid).
- 0.5 mg/mL vial: NDC 68547-005-01: A carton of one 1 mL single-dose vial containing 0.5 mg angiotensin II (as a sterile liquid).

16.2. Storage and Handling

- GIAPREZA vials should be stored in the refrigerator between 2°C to 8°C (36°F to 46°F).
- Discard prepared diluted solution after 24 hours at room temperature or under refrigeration.

Manufactured for:

La Jolla Pharmaceutical Company
Waltham, MA 02451 USA

GIAPREZA® is a registered trademark of La Jolla Pharmaceutical Company.

©2021, La Jolla Pharmaceutical Company. All rights reserved.